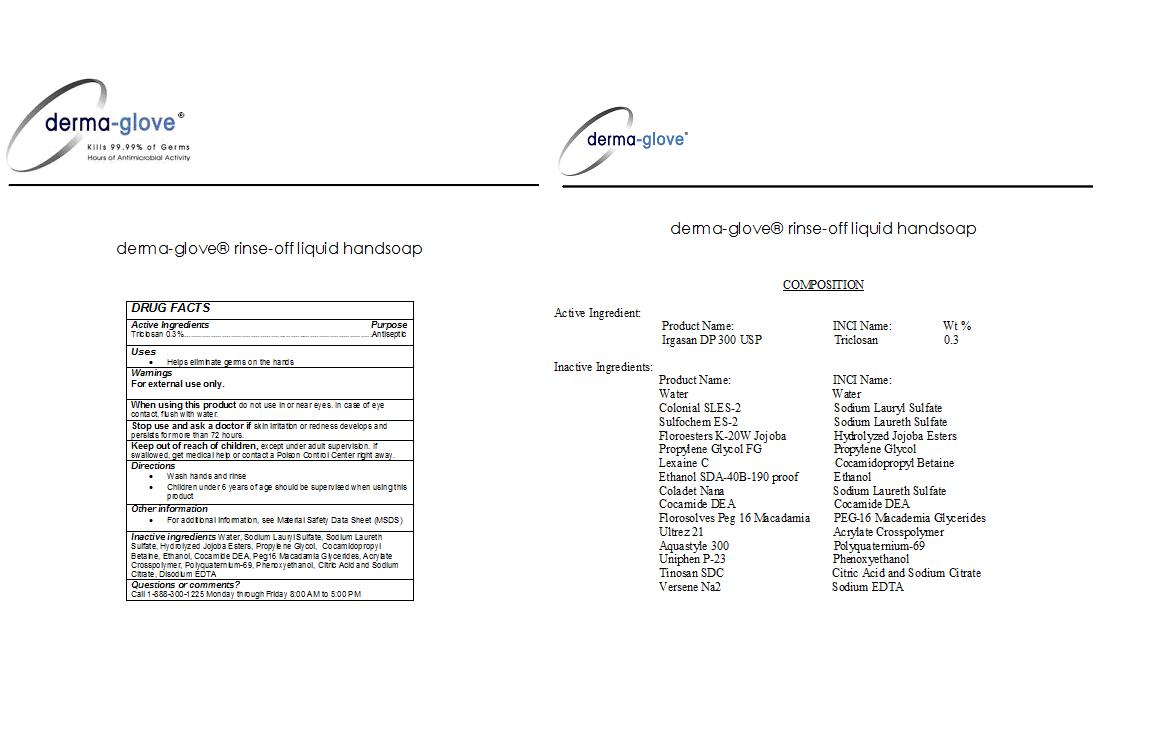 DRUG LABEL: Derma-Glove
NDC: 24673-247 | Form: SOAP
Manufacturer: RWM TECHNOLOGIES
Category: otc | Type: HUMAN OTC DRUG LABEL
Date: 20100601

ACTIVE INGREDIENTS: Triclosan .03 g/1 g

DERMA-GLOVE RINSE-OFF LIQUID HANDSOAP

DESCRIPTION

DERMA-GLOVE(R) rinse-off liquid handsoap

Active Ingredient

Triclosan 0.3%.............................................Antiseptic

PURPOSE

Antiseptic hand soap

INDICATIONS AND USAGE

- Helps eliminate germs on the hands

Warnings

For external use only.

When using this product do not use in or near eyes. In case of eye contact, flush with water.

Stop use and ask a doctor if skin irritation or redness develops and persists for more than 72 hours.

KEEP OUT OF REACH OF CHILDREN

Keep out of the Reach of Children, except under adult supervision. If swallowed, get medical help or contact a Poison Control Center right away.

Directions:

- Wash hands and rinse
- Children under 6 years of age should be supervised when using this product

GENERAL PRECAUTIONS

For additional information, see Material Safety Data Sheet (MSDS).

INACTIVE INGREDIENT

Water, Sodium Lauryl Sulfate, Sodium Laureth Sulfate, Hydrolyzed Jojoba Esters, Propylene Glycol, Cocamidopropyl Betaine, Ethanol, Cocamide DEA, Peg16 Macadamia Glycerides, Acrylate Crosspolymer, Polyquaternium-69, Phenoxyethanol, Citric Acid and Sodium Citrate, Disodium EDTA

Questions or Comments?

Call 1-888-300-1225 Monday through Friday 8:00 AM to 5:00 PM

LABEL